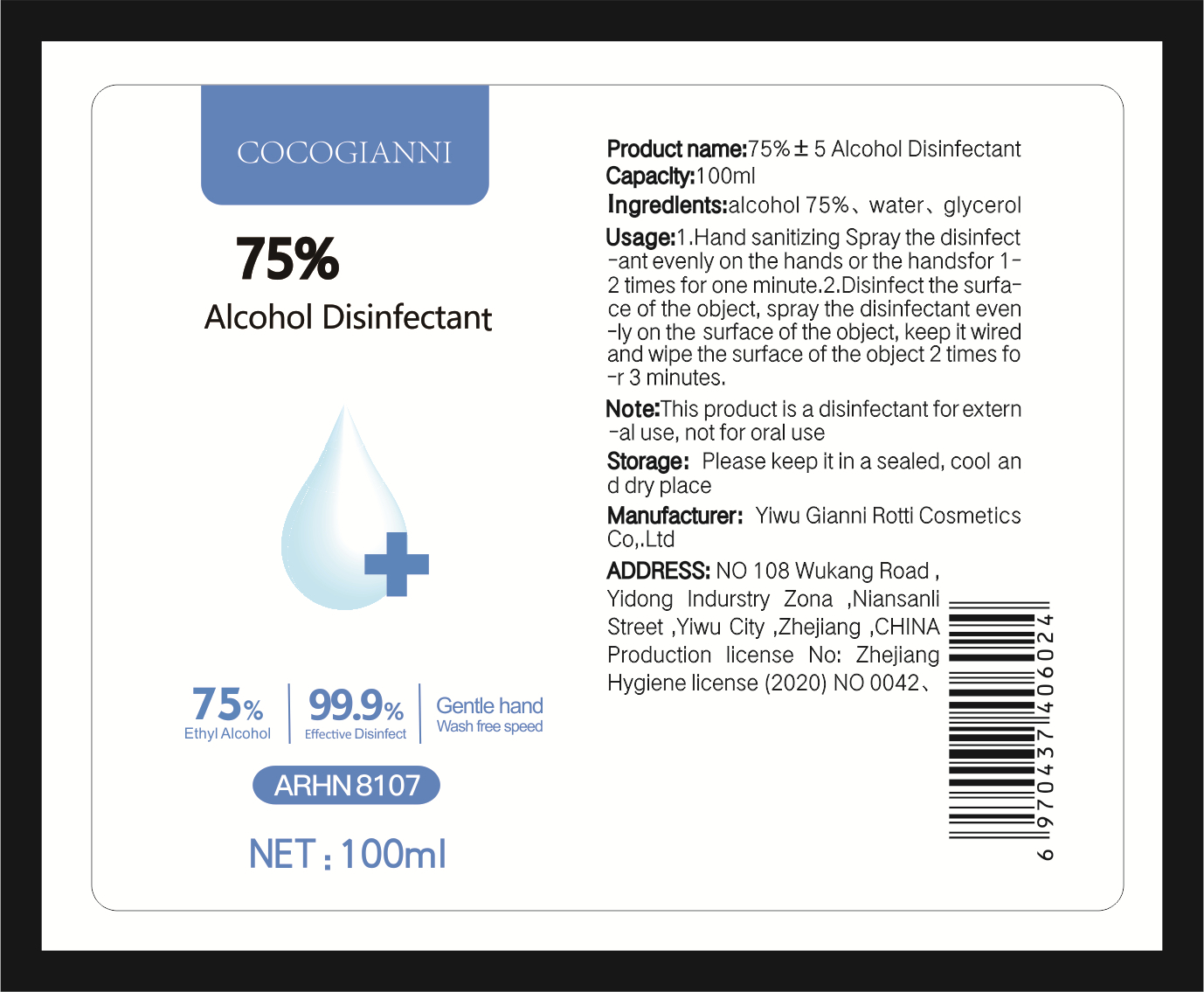 DRUG LABEL: 75% ALCOHOL DISINFECTANT
NDC: 54282-001 | Form: LIQUID
Manufacturer: YIWU GIANNI ROTTI COSMETICS CO., LTD.
Category: otc | Type: HUMAN OTC DRUG LABEL
Date: 20200410

ACTIVE INGREDIENTS: ALCOHOL 75 mL/100 mL
INACTIVE INGREDIENTS: GLYCERIN; WATER

ACTIVE INGREDIENT

alcohol

INACTIVE INGREDIENT

Water,glycerol

INDICATIONS AND USAGE

Hand sanitizing Spray the disinfectant evenly on the hands or the handsfor 1 -2 times for one minute.

Disinfect the surface of the object, spray the disinfectant evenly on the surface of the object, keep it wired and wipe the surface of the object 2 times for 3 minutes.

DOSAGE AND ADMINISTRATION

Please keep it in a sealed, cool and dry place

WARNINGS

This product is a disinfectant for external use, not for oral use

PURPOSE

Disinfection
Sterilization
No Rinseing

keep out of reach of children